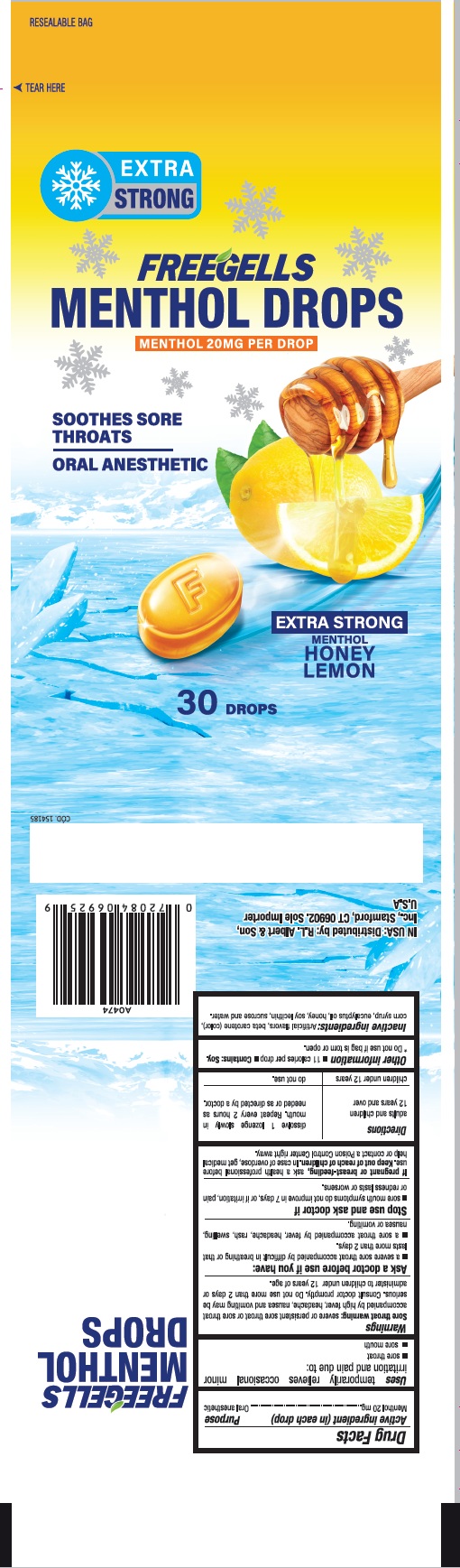 DRUG LABEL: Menthol Drops Freegells Extra Strong Honey Lemon 30ct
NDC: 83002-012 | Form: LOZENGE
Manufacturer: R.L. ALBERT & SON, INC
Category: otc | Type: HUMAN OTC DRUG LABEL
Date: 20251104

ACTIVE INGREDIENTS: MENTHOL 20 mg/1 1
INACTIVE INGREDIENTS: SUCROSE; CORN SYRUP; EUCALYPTOL; LECITHIN, SOYBEAN; HONEY; BETA CAROTENE

Drug Facts

Active ingredient

Menthol 20 mg

Purpose

Oral anesthetic

Use

Temporarily relieves occasional minor irritation and pain due to:

- sore throat
- sore mouth

Warning

Sore throat warning: severe or persistent sore throat or sore throat accompanied by high fever, headache, nausea, and vomiting may be serious. Consult a doctor promptly. Do not use more than 2 days or administer to children under 12 years of age.

Ask a doctor before use if you have :

- a severe sore throat accompanied by difficult in breathing or that lasts more than 2 days.
- a sore throat accompanied by fever, headache, rash, swelling, nausea or vomiting.

Stop use and ask doctor if

- sore mouth symptoms do not improve in 7 days or if irritation, pain or redness lasts or worsens

If pregnant or breast-feeding, ask a health professional before use.

Directions

Adults and children 12 years and over | dissolve 1 lozenge slowly in mouth. Repeat every 2 hours as needed or as directed by a doctor
children under 12 years | do not use.

Other information

- 11 calories per drop
- Do not use if the bag is torn or open.
- Contains: Soy

Inactive ingredients

Artificial flavors, beta carotene, corn syrup, eucalyptus oil, honey , Soy Lecithin, sucrose and water.